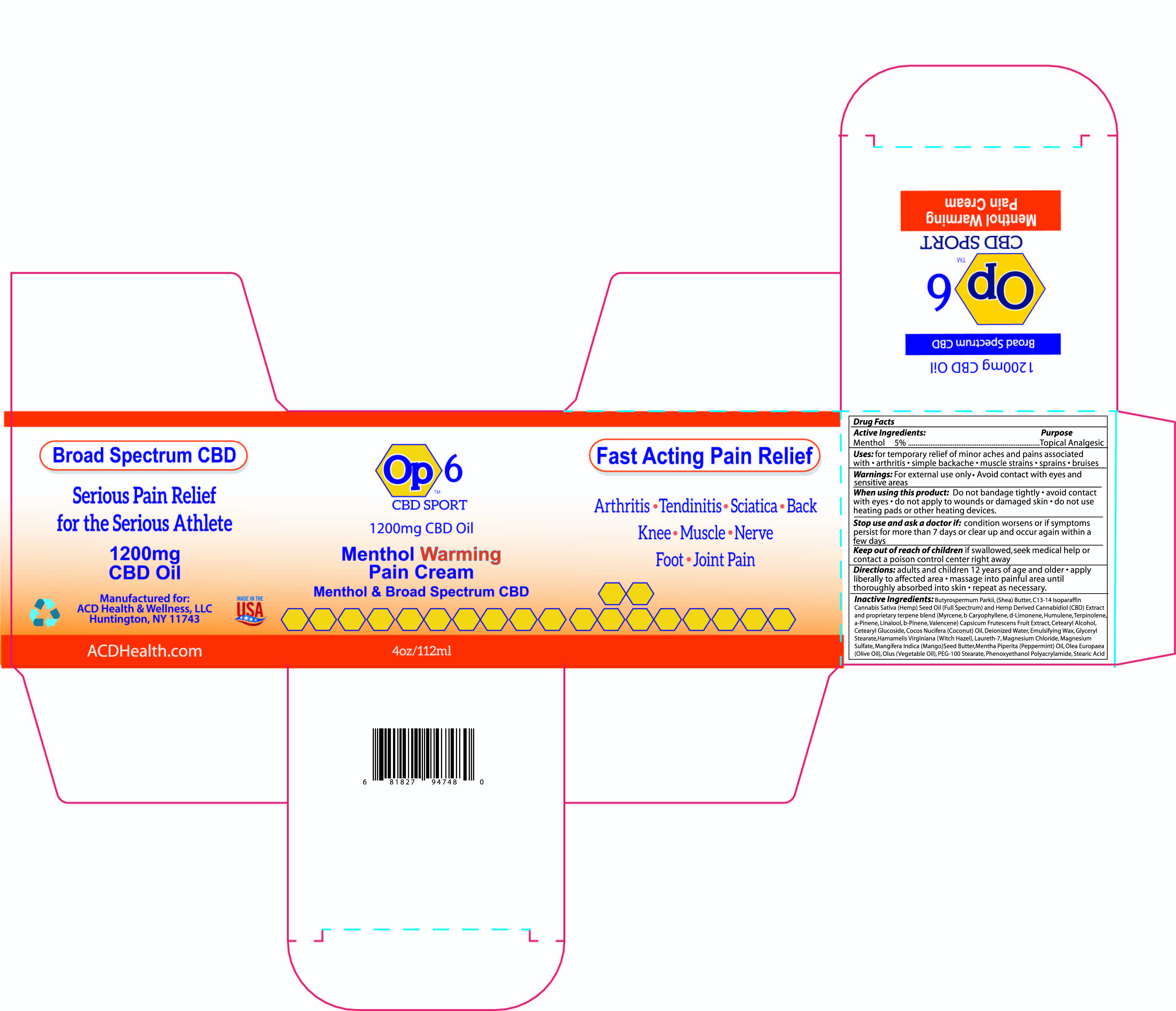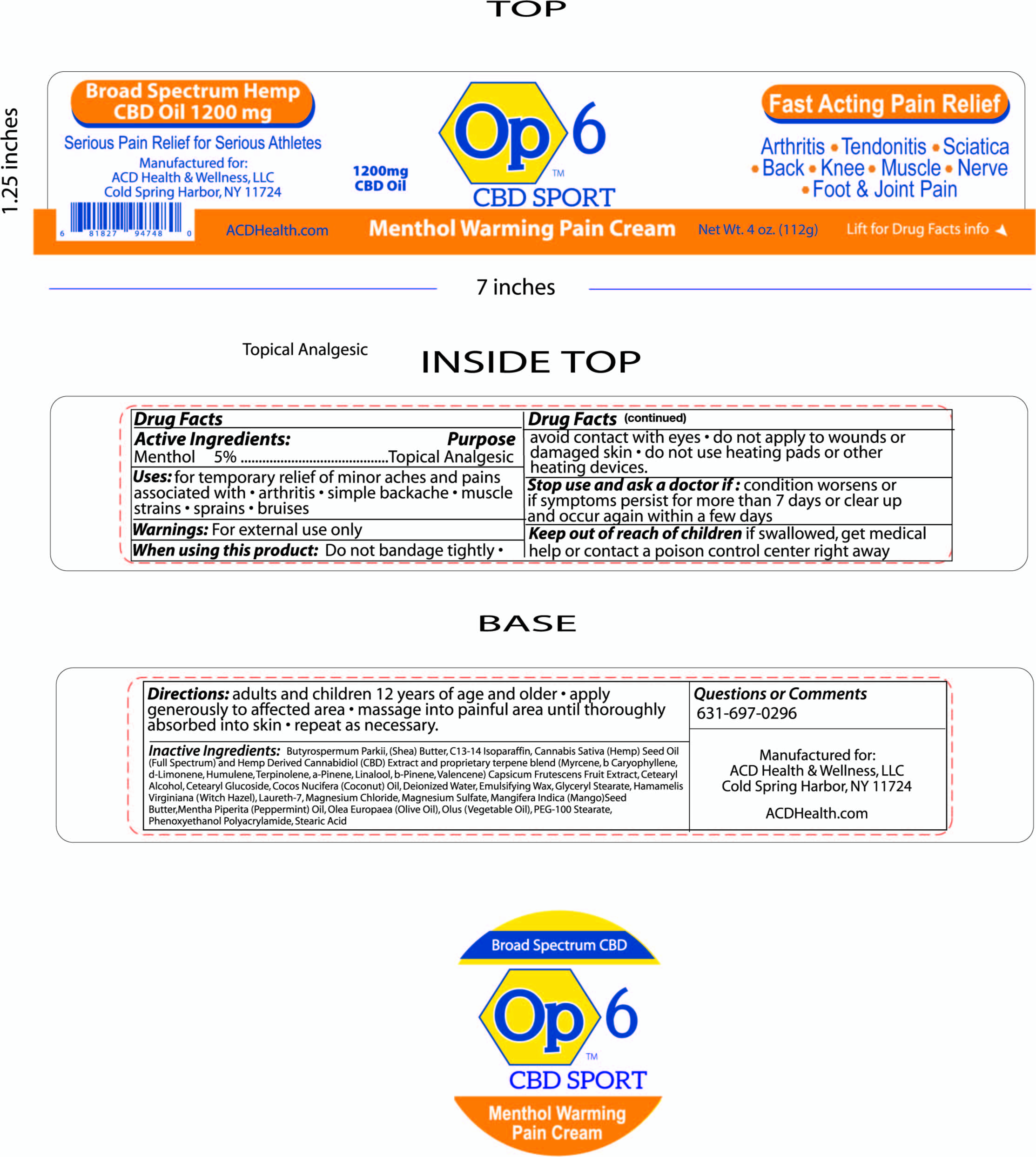 DRUG LABEL: op6 Menthol Warming Pain Cream
NDC: 76348-681 | Form: CREAM
Manufacturer: Renu Laboratories, Inc.
Category: otc | Type: HUMAN OTC DRUG LABEL
Date: 20210914

ACTIVE INGREDIENTS: MENTHOL 5.6 g/112 g
INACTIVE INGREDIENTS: TABASCO PEPPER; .BETA.-PINENE; HUMULENE; TERPINOLENE; LINALOOL, (+)-; VALENCENE; CANNABIDIOL; WATER; POLYETHYLENE GLYCOL 4500; CORN OIL; MANGIFERA INDICA SEED BUTTER; PEPPERMINT OIL; PHENOXYETHANOL; POLYACRYLAMIDE (10000 MW); GLYCERYL MONOSTEARATE; CETEARYL GLUCOSIDE; COCONUT OIL; WHITE WAX; SHEA BUTTER; C13-14 ISOPARAFFIN; CANNABIS SATIVA SEED OIL; CETOSTEARYL ALCOHOL; OLIVE OIL; STEARIC ACID; GRAPEFRUIT OIL; MAGNESIUM CHLORIDE; MAGNESIUM SULFATE, UNSPECIFIED; LAURETH-7; WITCH HAZEL; MYRCENE; LIMONENE, (+)-; CARYOPHYLLENE; .ALPHA.-PINENE

op6 Menthol Warming Pain Cream

ACTIVE INGREDIENT

Menthol 5 percent

Warnings

For external use only

When using this product do not bandage tightly

avoid contact with eye

do not apply to wounds or damaged skin

Stop use and ask doctor

if condition worsens or if symptoms persist for more than 7 days or clear up and occur again within a few days

Keep out of reach of children

If swallowed get medical help or contact Poison Control Center right away

Keep out of reach of children. If swallowed get medical help or contact a Poison Control center right away.

PURPOSE

Topical Analgesic

Directions

adults and children 12 years of age and older

apply generously to affected area

massage into painful area until thoroughly absorbed into skin

repeat as necessary

INACTIVE INGREDIENT

Butyrospermum Parkii (Shea) Butter, C13-14 Isoparaffin, Cannabis Sativa (Hempseed) Oil and Hemp Derived Cannabidiol (CBD) Extract and proprietary terpene blend (Myrcene, b-Caryophyllene, d-Limonene, Humulene, Terpinolene, a-Pinene, Linalool, b-Pinene, Valencene, Cetearyl Alcohol, Cetearyl Glucoside, Cocos Nucifera (Coconut) Oil, Deionized Water, Emulsifying Wax, Glyceryl Stearate, Grapefruit Oil, Hamamelis Virginiana (Witch Hazel), Laureth-7, Magnesium Chloride, Magnesium Sulfate, Mangifera Indica (Mango) Seed Butter, Mentha Piperita (Peppermint) Oil, Olea Europaea (Olive) Oil, Olus (Vegetable) Oil, PEG-100, Phenoxyethanol, Polyacrylamide, Stearic Acid

Uses

for temporary relief of minor aches and pains asssociated with

arthritis

simple backache

muscle strains

sprains

bruises

RECENT MAJOR CHANGES

SIMPLE DATE CHANGE

Nothing considered as major

QUESTIONS OR COMMENTS

631 697 0296

ACD HEALTH AND WELLNESS LLC

ACDHEALTH.COM

PRODUCT LABEL AND BOX ART